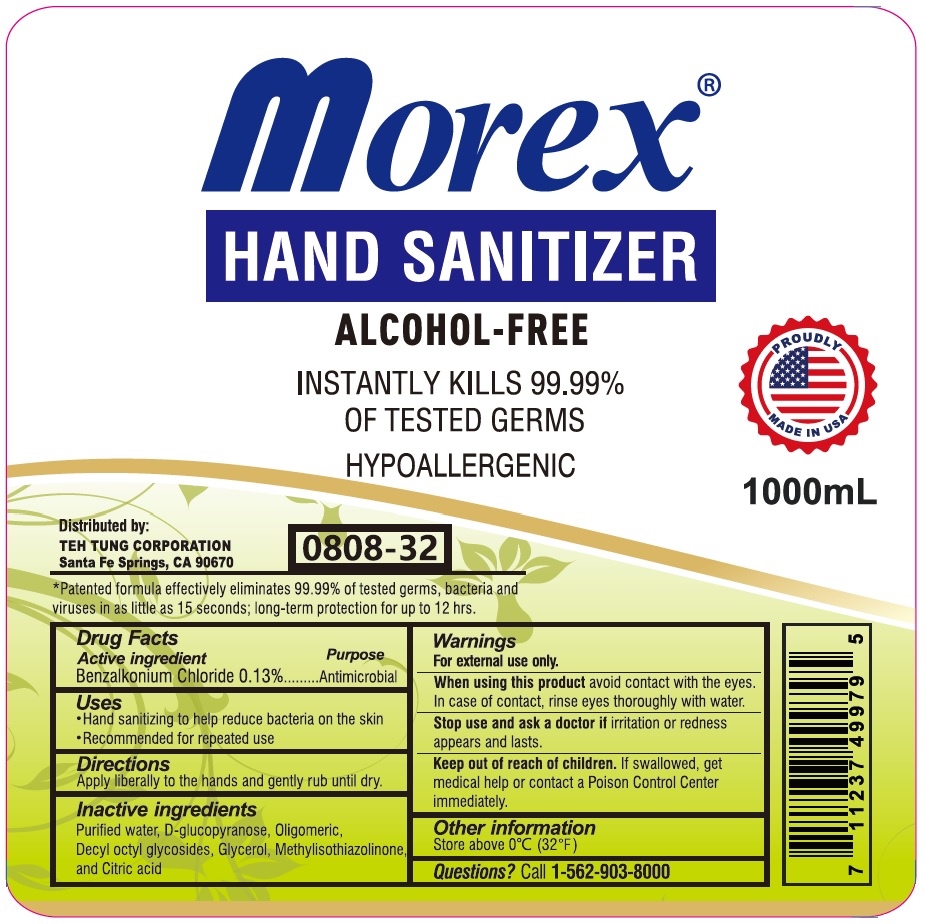 DRUG LABEL: Morex HAND SANITIZER
NDC: 78168-608 | Form: SOLUTION
Manufacturer: Teh Tung Corporation
Category: otc | Type: HUMAN OTC DRUG LABEL
Date: 20201006

ACTIVE INGREDIENTS: BENZALKONIUM CHLORIDE 0.13 g/100 mL
INACTIVE INGREDIENTS: WATER; 2,3 DI-O-METHYL-D-GLUCOSE; CAPRYL OLIGOGLUCOSIDE; CAPRYLYL/CAPRYL OLIGOGLUCOSIDE; GLYCERIN; METHYLISOTHIAZOLINONE; CITRIC ACID MONOHYDRATE

Morex® HAND SANITIZER

Active ingredient

Benzalkonium Chloride 0.13%

Purpose

Antimicrobial

Uses

• Hand sanitizing to help reduce bacteria on the skin

• Recommended for repeated use

Directions

Apply liberally to the hands and gently rub until dry.

Inactive ingredients

Purified water, D-glucopyranose, Oligomeric, Decyl octyl glycosides, Glycerol, Methylisothiazolinone, and Citric acid

Warnings

For external use only.

When using this product avoid contact with the eyes. In case of contact, rinse eyes thoroughly with water.

Stop use and ask a doctor if irritation or redness appears and lasts.

Keep out of reach of children. If swallowed, get medical help or contact a Poison Control Center immediately.

Other information

Store above 0°C (32°F)

Questions? Call 1-562-903-8000

ALCOHOL-FREE

INSTANTLY KILLS 99.99% OF TESTED GERMS

HYPOALLERGENIC

PROUDLY MADE IN USA

Distributed by:

TEH TUNG CORPORATION

Santa Fe Springs, CA 90670

*Patented formula effectively eliminates 99.99% of tested germs, bacteria and viruses in as little as 15 seconds; long-term protection for up to 12 hrs.